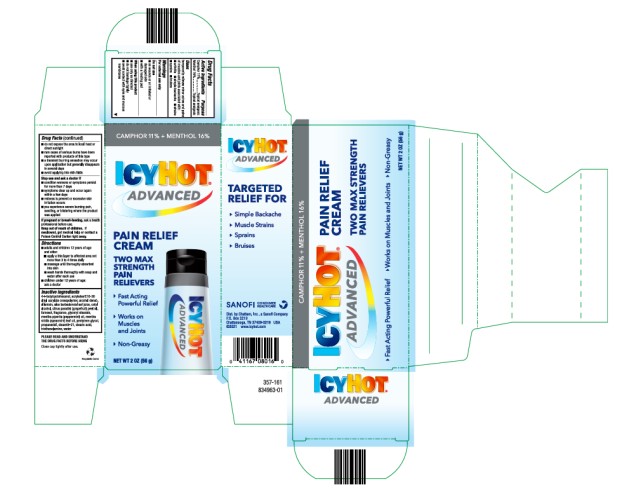 DRUG LABEL: Icy Hot Advanced Relief
NDC: 41167-0801 | Form: CREAM
Manufacturer: Chattem, Inc.
Category: otc | Type: HUMAN OTC DRUG LABEL
Date: 20240301

ACTIVE INGREDIENTS: CAMPHOR (SYNTHETIC) 0.11 g/1 g; MENTHOL 0.16 g/1 g
INACTIVE INGREDIENTS: 4-TERT-BUTYLCYCLOHEXANOL; ACRYLATES/C10-30 ALKYL ACRYLATE CROSSPOLYMER (60000 MPA.S); ALCOHOL; ALLANTOIN; ALOE VERA LEAF; CETYL ALCOHOL; CITRUS PARADISI (GRAPEFRUIT) PEEL OIL; FARNESOL; GLYCERYL STEARATE; MENTHA PIPERITA (PEPPERMINT) OIL; MENTHA VIRIDIS (SPEARMINT) LEAF OIL; PENTYLENE GLYCOL; PROPANEDIOL; STEARETH-21; STEARIC ACID; TRIETHANOLAMINE; WATER

Icy Hot Advanced Relief Cream

Drug Facts

Active ingredients

Menthol 16%

Camphor 11%

Purpose

Topical analgesic

Uses

Temporarily relieves minor aches and pains of muscles and joints associated with:

- arthritis
- simple backache
- strains
- sprains
- bruises

Warnings

For external use only

Do not use

■ on wounds or on irritated or damaged skin

■ with a heating pad

When using this product

- use only as directed
- do not bandage tightly
- avoid contact with eyes and mucous membranes
- do not expose the area to local heat or direct sunlight
- rare cases of serious burns have been reported with products of this type
- a transient burning sensation may occur upon application but generally disappears in several days
- avoid applying into skin folds

Stop use and ask a doctor if

- condition worsens or symptoms persist for more than 7 days
- symptoms clear up and occur again within a few days
- redness is present or excessive skin irritation occurs
- you experience severe burning pain, swelling, or blistering where the product was applied

If pregnant of breast feeding,

ask a health professional before use.

Keep out of reach of children.

If swallowed, get medical help or contact a Poison Control Center right away.

Directions

■ adults and children 12 years of age and older:

■ apply a thin layer to affected area not more than 3 to 4 times daily

■ massage until thoroughly absorbed into skin

■ wash hands thoroughly with soap and water after each use

■ children under 12 years of age: ask a doctor

Inactive ingredients

4-t-butylcyclohexanol, acrylates/C10-30 alkyl acrylate crosspolymer, alcohol denat., allantoin, aloe barbadensis leaf juice, cetyl alcohol, citrus paradisi (grapefruit) peel oil, farnesol, fragrance, glyceryl stearate, mentha piperita (peppermint) oil, mentha viridis (spearmint) leaf oil, pentylene glycol, propanediol, steareth-21, stearic acid, triethanolamine, water

Principal Display Panel

ICY HOT®
ADVANCED
PAIN RELIEF
CREAM
NET WT 2 OZ (56 g)